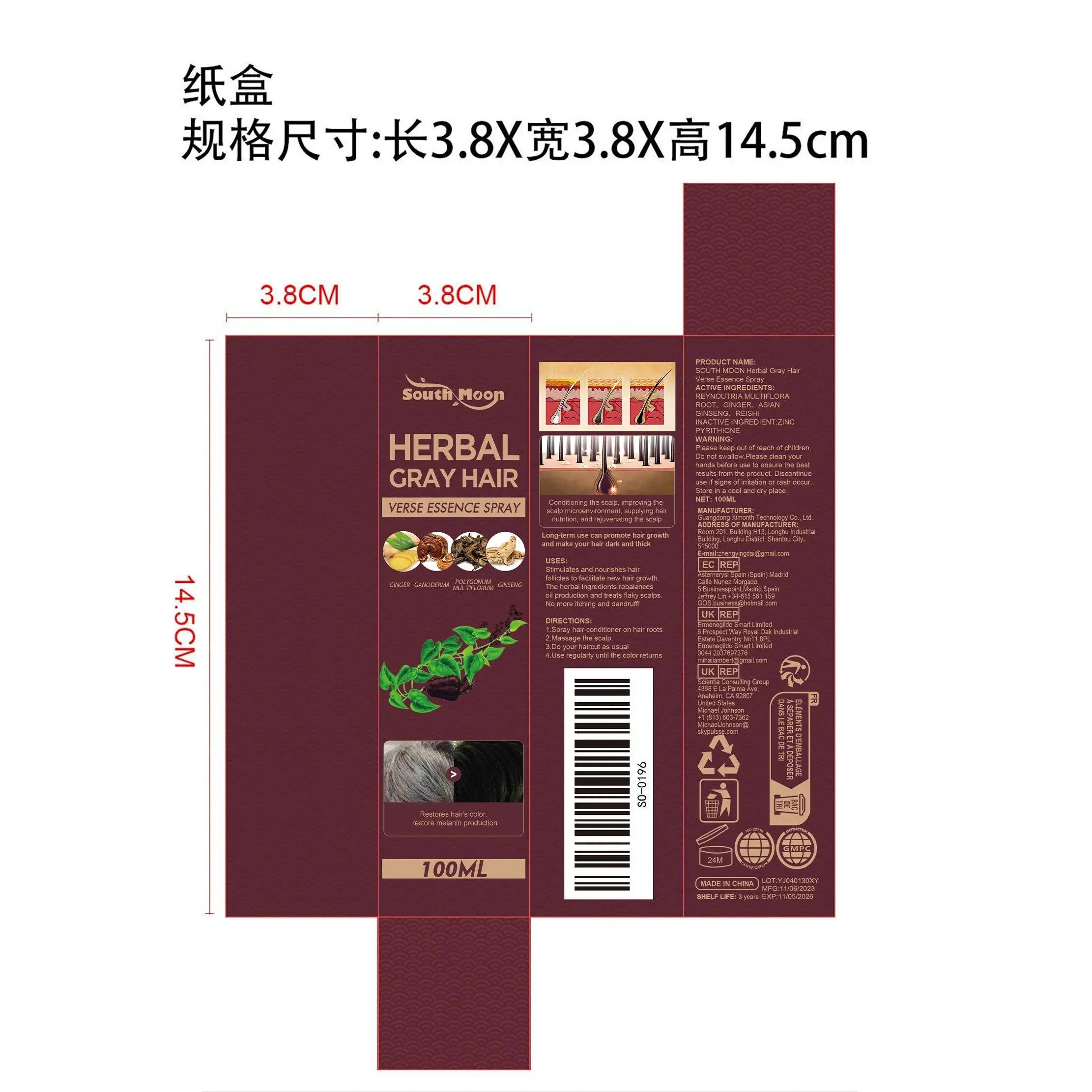 DRUG LABEL: SOUTH MOON Herbal Gray Hair Verse Essence
NDC: 84660-049 | Form: LIQUID
Manufacturer: Guangdong Ximonth Technology Co., Ltd.
Category: otc | Type: HUMAN OTC DRUG LABEL
Date: 20241028

ACTIVE INGREDIENTS: REYNOUTRIA MULTIFLORA ROOT 10 mg/100 mg; GINGER 5 mg/100 mg; REISHI 20 mg/100 mg; ASIAN GINSENG 25 mg/100 mg
INACTIVE INGREDIENTS: ZINC PYRITHIONE 40 mg/100 mg

Active Ingredient(s)

REYNOUTRIA MULTIFLORA ROOT、GINGER、ASIAN GINSENG、REISHI

Purpose

Stimulates and nourishes hair follicles to facilitate new hair growth. The herbal ingredients rebalances oil production and treats flaky scalps. No more itching and dandruff

Use

1.Spray hair conditioner on hair roots
2.Massage the scalp
3.Do your haircut as usual
4.Use regularly until the color returns

Warnings

Please keep out of reach of children.Do not swallow.Please clean your hands before use to ensure the best results from the product.Discontinue use if signs of irritation or rash occur.Store in a cool and dry place.

Do not use

Discontinue use if signs of irritation or rash occur.

Stop Use

Discontinue use if signs of irritation or rash occur.

KEEP OUT OF REACH OF CHILDREN

Please keep out of reach of children. Do not swallow.

STORAGE AND HANDLING

Store in a cool and dry place.

INACTIVE INGREDIENT

ZINC PYRITHIONE